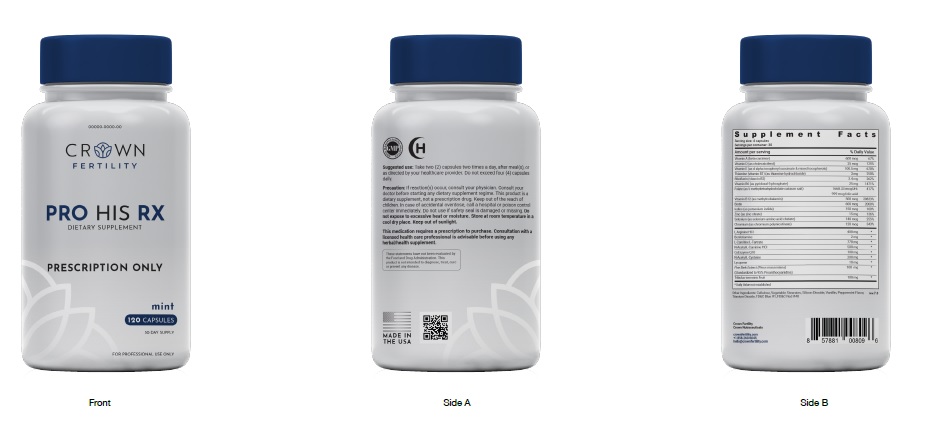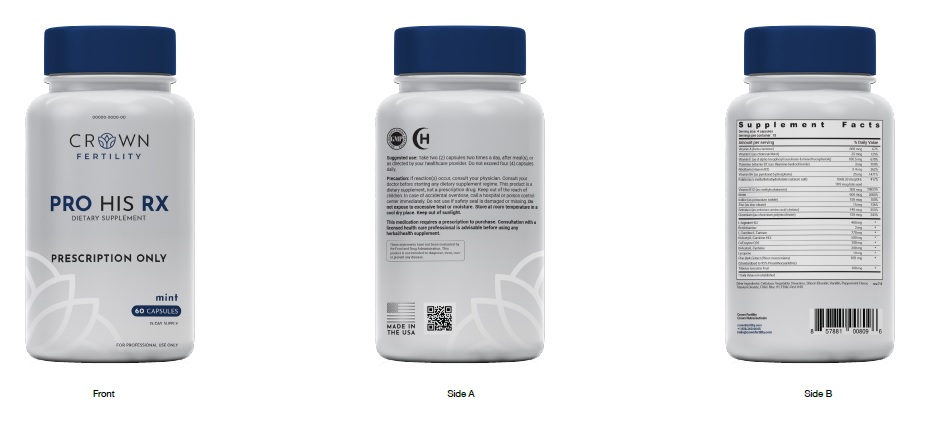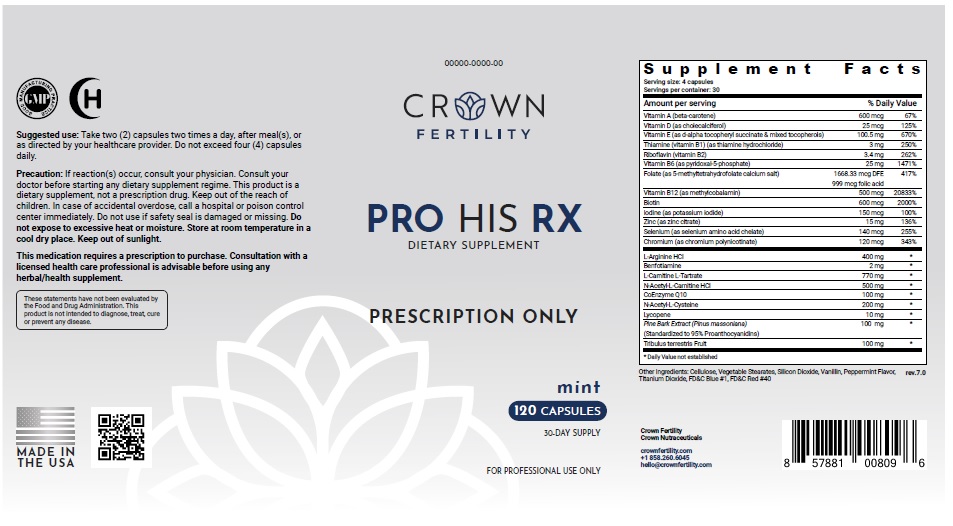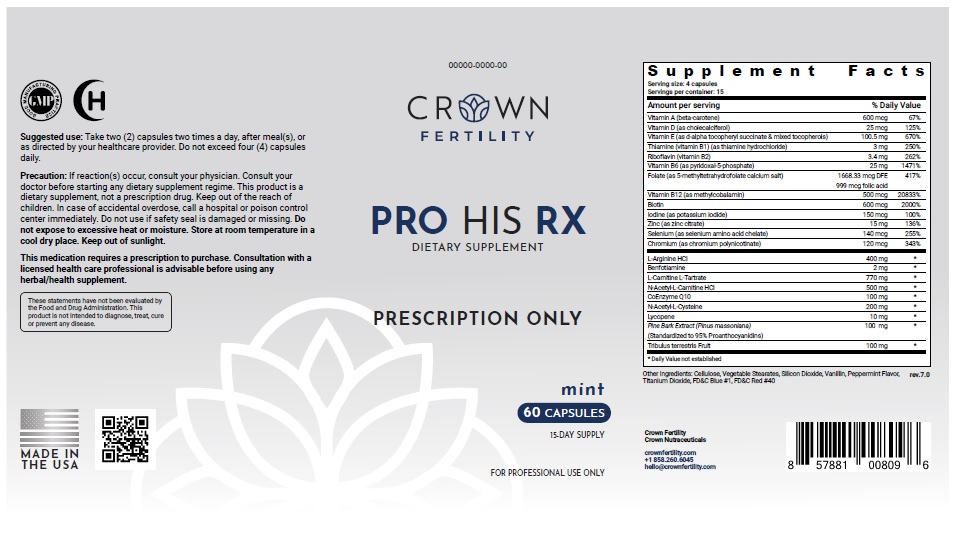 DRUG LABEL: PRO HIS MINT
NDC: 73489-002 | Form: CAPSULE
Manufacturer: CROWN GENERAL AGENCY INC
Category: other | Type: Dietary Supplement
Date: 20211021

ACTIVE INGREDIENTS: VITAMIN A 600 ug/1 1; CHOLECALCIFEROL 25 ug/1 1; .ALPHA.-TOCOPHEROL ACETATE 100.5 mg/1 1; THIAMINE 3 mg/1 1; RIBOFLAVIN 3.4 mg/1 1; PYRIDOXINE HYDROCHLORIDE 25 mg/1 1; FOLIC ACID 999 ug/1 1; CYANOCOBALAMIN 500 ug/1 1; BIOTIN 600 ug/1 1; IODINE 150 ug/1 1; ZINC 15 mg/1 1; SELENIUM 140 ug/1 1; CHROMIUM 120 ug/1 1
INACTIVE INGREDIENTS: POWDERED CELLULOSE; MAGNESIUM STEARATE; SILICON DIOXIDE; 2,2-BIS(4-HYDROXY-3-TERT-BUTYLPHENYL)PROPANE

STATEMENT OF IDENTITY

Dietary Supplement

Suggested Use

Take two (2) capsules two times a day, after meal(s), or as directed by your healthcare provider. Do not exceed four (4) capsules daily.

Precaution

If reaction(s) occur, consult your physician. Consult your doctor before starting any dietary supplement regime. This product is a dietary supplement, not a prescription drug. Keep out of the reach of children. In case of accidental overdose, call a hospital or poison control center immediately. Do not use if safety seal is damaged or missing. Do not expose to excessive heat or moisture. Store at room temperature in a cool dry place. Keep out of sunlight.